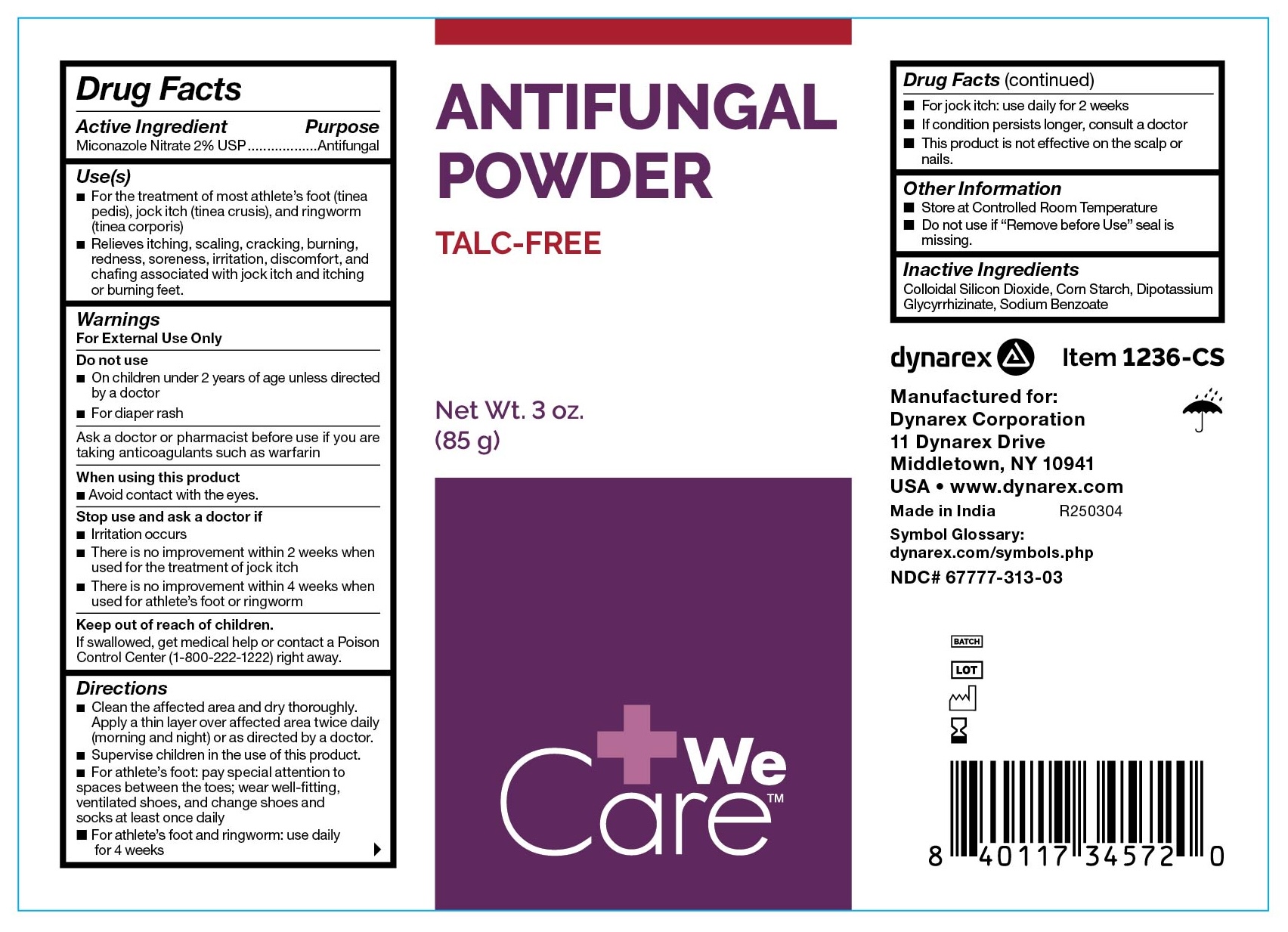 DRUG LABEL: 1236-CS Antifungal Powder (Talc Free)
NDC: 67777-313 | Form: POWDER
Manufacturer: Dynarex Corporation
Category: otc | Type: HUMAN OTC DRUG LABEL
Date: 20250325

ACTIVE INGREDIENTS: MICONAZOLE NITRATE 20 mg/1 g
INACTIVE INGREDIENTS: STARCH, CORN; SILICON DIOXIDE; GLYCYRRHIZINATE DIPOTASSIUM; SODIUM BENZOATE

1236-CS Antifungal Powder (Talc Free)

Active Ingredient

Miconazole Nitrate 2% USP

Purpose

Antifungal

Use(s)

• For the treatment of most athlete's foot (tinea pedis), jock itch (tinea crusis), and ringworm (tinea corporis)

• Relieves itching, scaling, cracking, burning, redness, soreness, irritation, discomfort, and chafing associated with jock itch and itching or burning feet.

Warnings

For External Use Only

Do not use

• On children under 2 years of age unless directed by a doctor

• For diaper rash

Ask a doctor or pharmacist

Before use if you are taking anticoagulants such as warfarin

When using this product

• Avoid contact with the eyes

Stop use and ask a doctor if

• Irritation occurs

• There is no improvement within 2 weeks when used for the treatment of jock itch

• There is no improvement within 4 weeks when used for athlete's foot or ringworm

Keep out of reach of children

If swallowed, get medical help or contact a Poison Control Center (1-800-222-1222) right away.

Directions

• Clean the affected area and dry thoroughly. Apply a thin layer over the affected area twice daily (morning and night) or as directed by a doctor.

• Supervise children in the use of this product.

• For athlete's foot: pay special attention to spaces between the toes; wear well-fitting, ventilated shoes, and change shoes and socks at least once daily

• For athlete's foot and ringworm: use daily for 4 weeks

• For jock itch: use daily for 2 weeks

• If condition persists longer, consult a doctor

• This product is not effective on the scalp or nails

Other Information

• Store at Controlled Room Temperature • Do not use if "Remove before Use" seal is missing

Inactive Ingredients

Colloidal Silicon Dioxide, Corn Starch, Dipotassium Glycyrrhizinate, Sodium Benzoate

Questions?

1-888-396-2739 Monday - Friday 9AM - 5PM EST

Label

1236-CS Antifungal Powder (Talc Free)